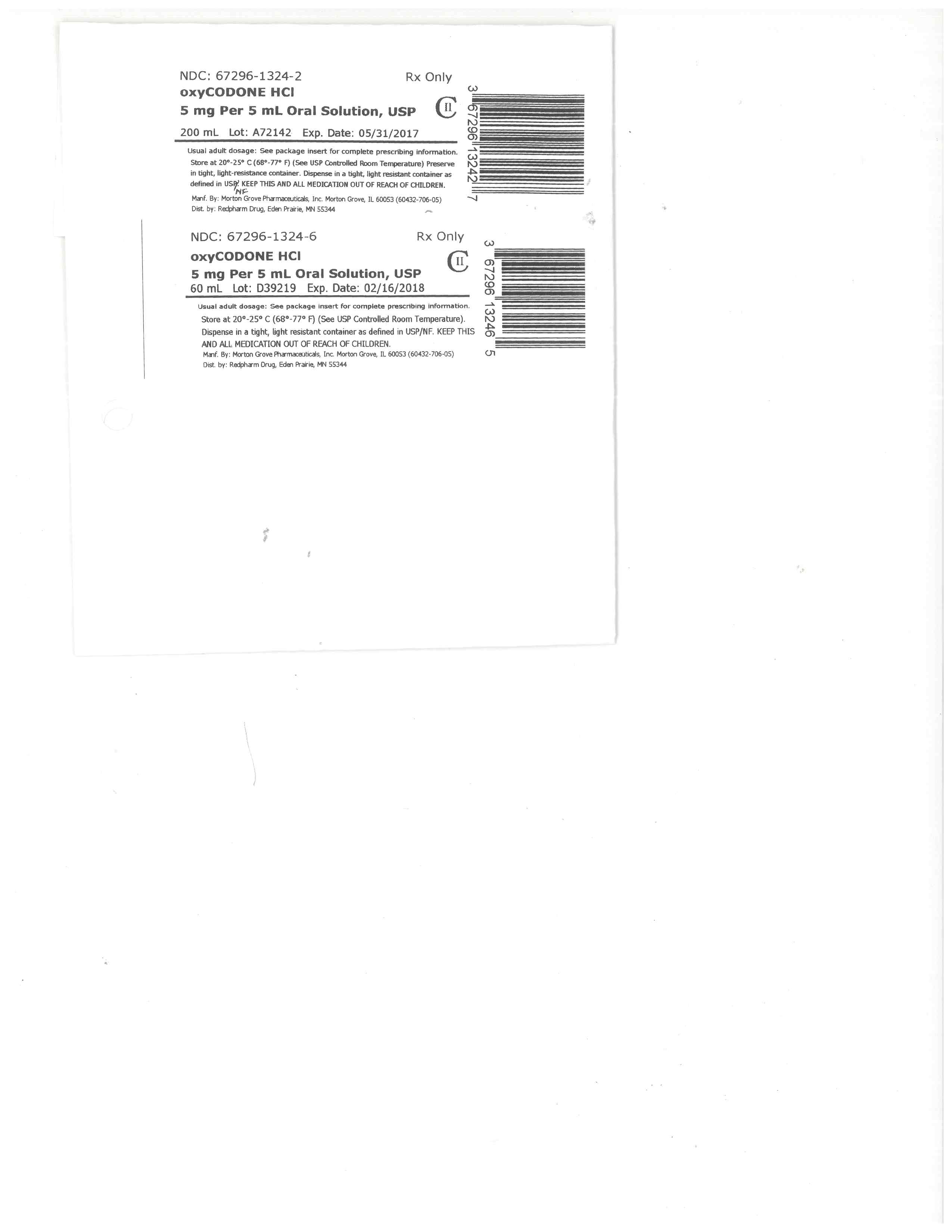 DRUG LABEL: Oxycodone Hydrochloride
NDC: 67296-1324 | Form: SOLUTION
Manufacturer: RedPharm Drug, Inc.
Category: prescription | Type: HUMAN PRESCRIPTION DRUG LABEL
Date: 20220120
DEA Schedule: CII

ACTIVE INGREDIENTS: OXYCODONE HYDROCHLORIDE 5 mg/5 mL
INACTIVE INGREDIENTS: ANHYDROUS CITRIC ACID; SORBITOL; RASPBERRY; WATER; FD&C RED NO. 40; GLYCERIN; POLOXAMER 188; SODIUM BENZOATE

BOXED WARNING

Take care when prescribing and administering Oxycodone Hydrochloride Oral Solution, USP 5 mg per 5 mL to avoid dosing errors due to confusion between mg and mL, and other oxycodone ...

WARNING: RISK OF MEDICATION ERRORS

Take care when prescribing and administering Oxycodone Hydrochloride Oral Solution, USP 5 mg per 5 mL to avoid dosing errors due to confusion between mg and mL, and other oxycodone solutions with different concentrations, which could result in accidental overdose and death.

Take care to ensure the proper dose is communicated and dispensed.

Keep Oxycodone Hydrochloride Oral Solution, USP out of the reach of children. In case of accidental ingestion, seek emergency medical help immediately.

HIGHLIGHTS OF PRESCRIBING INFORMATION

These highlights do not include all the information needed to use Oxycodone Hydrochloride Oral Solution, USP safely and effectively. See full prescribing information for Oxycodone Hydrochloride Oral Solution, USP.
Oxycodone Hydrochloride Oral Solution, USP CII
Initial U.S. Approval: 1950

WARNING: RISK OF MEDICATION ERRORS
TAKE CARE WHEN PRESCRIBING AND ADMINISTERING OXYCODONE HYDROCHLORIDE ORAL SOLUTION, USP 5 MG PER 5 ML TO AVOID DOSING ERRORS DUE TO CONFUSION BETWEEN MG AND ML, AND OTHER OXYCODONE SOLUTIONS WITH DIFFERENT CONCENTRATIONS, WHICH COULD RESULT IN ACCIDENTAL OVERDOSE AND DEATH.

Take care to ensure the proper dose is communicated and dispensed.

Keep Oxycodone Hydrochloride Oral Solution, USP out of the reach of children. In case of accidental ingestion, seek emergency medical help immediately.

INDICATIONS AND USAGE

Oxycodone Hydrochloride Oral Solution, USP is an opioid agonist indicated for the management of moderate to severe pain where the use of an opioid analgesic is appropriate. (1)

DOSAGE AND ADMINISTRATION

Dosage should be individualized based on the severity of pain, and patient response. (2.1)
Patients who have not been receiving opioid analgesics should be started in dosing range of 5 to 15 mg every 4 to 6 hours as needed. (2.2)
When converting from a fixed ratio opioid/non-opioid regimen, the dose should be titrated in response to the level of analgesia and adverse effects and depending on continuation or non-continuation of the non-opioid component. (2.3)
In patients with hepatic impairment or end-stage renal failure, dose initiation should follow a conservative approach. (2.7)

DOSAGE FORMS AND STRENGTHS

Oral Solution containing 5 mg per 5 mL oxycodone hydrochloride, available in 500 mL bottle and 5 mL unit dose cup. (3)

CONTRAINDICATIONS

Respiratory depression in the absence of resuscitative equipment. (4)
Suspected or confirmed paralytic ileus. (4)
Acute or severe bronchial asthma or hypercarbia. (4)
Known hypersensitivity to oxycodone. (4)

WARNINGS AND PRECAUTIONS

Use caution when prescribing, dispensing, and administering Oxycodone Hydrochloride Oral Solution, USP to avoid dosing errors due to confusion between different concentrations and between mg and mL, which could result in accidental overdose and death. (5.1)
Increased risk or respiratory depression in elderly, debilitated patients, those suffering from conditions accompanied by hypoxia, hypercapnea, or upper airway obstruction. (5.2)
Oxycodone hydrochloride is a Schedule II controlled substance with an abuse liability similar to other opioids. (5.3)
Assess patients for their clinical risks for opioid abuse or addiction prior to being prescribed opioids. (5.3)
Additive CNS depressive effects when used in conjunction with alcohol, other opioids, or illicit drugs. (5.4)
Increased risk of respiratory depression and of elevation of cerebrospinal fluid pressure in patients with head injury, intracranial lesions or pre-existing increase in intracranial pressure. (5.5)
Risk of severe hypotension in patients with compromised ability to maintain blood pressure. (5.6)
May obscure the diagnosis or clinical course in patients with acute abdominal conditions. (5.7)
Use with caution in patients with biliary tract disease and acute pancreatitis. (5.8)
The mental and/or physical abilities required for the performance of potentially hazardous tasks such as driving a car or operating machinery may be impaired. (5.10)
Concomitant use of CYP3A4 inhibitors may increase opioid effects. (5.11)

ADVERSE REACTIONS

The most common adverse reactions are nausea, constipation, vomiting, headache, pruritus, insomnia, dizziness, asthenia, and somnolence. (6)

To report SUSPECTED ADVERSE REACTIONS CONTACT FDA at 1-800-FDA-1088 or www.fda.gov/medwatch.

DRUG INTERACTIONS

Skeletal muscle relaxants: Enhance action of and increased degree of respiratory depression (7.2)
Drugs that inhibit CYP3A4 activity may decrease clearance of oxycodone and lead to an increase in oxycodone plasma concentrations. (7.4)

USE IN SPECIFIC POPULATIONS

Safety and efficacy in pediatric patients below the age of 18 have not been established. (8.4)
Geriatric patients, Renal Impairment, and Hepatic impairment: Use caution during dose selection, starting at the low end of the dosing range while carefully monitoring for side effects. (8.5, 8.6, 8.7)

See 17 for PATIENT COUNSELING INFORMATION and Medication Guide.

Revised: 6/2015

FULL PRESCRIBING INFORMATION: CONTENTS*

WARNING: RISK OF MEDICATION ERRORS
1. INDICATIONS AND USAGE
2. DOSAGE AND ADMINISTRATION
2.1 Individualization of Dosage
2.2 Initiation of Therapy
2.3 Conversion to Oral Oxycodone Oral Solution
2.4 Conversion from Oral Oxycodone Hydrochloride to Controlled-Release Oral Oxycodone
2.5 Maintenance of Therapy
2.6 Cessation of Therapy
2.7 Dosage in patients with Hepatic or Renal Impairment
3. DOSAGE FORMS AND STRENGTHS
4. CONTRAINDICATIONS
5. WARNINGS AND PRECAUTIONS
5.1 Risk of Medication Errors
5.2 Respiratory Depression
5.3 Misuse and Abuse of Opioids
5.4 Interactions with Alcohol and Drugs of Abuse
5.5 Use in Head Injury and Increased Intracranial Pressure
5.6 Hypotensive Effect
5.7 Gastrointestinal Effects
5.8 Use in Pancreatic/Biliary Tract Disease
5.9 Special Risk Groups
5.10 Driving and Operating Machinery
5.11 Cytochrome P450 3A4 Inhibitors and Inducers
5.12 Seizures
6. ADVERSE REACTIONS
7. DRUG INTERACTIONS
7.1 CNS Depressants
7.2 Neuromuscular Blocking Agents
7.3 Mixed Agonist/Antagonist Opioid Analgesics
7.4 Agents Affecting Cytochrome P450 Enzymes
7.5 Monoamine Oxidase Inhibitors (MAOIs)
7.6 Anticholinergics
8. USE IN SPECIFIC POPULATIONS
8.1 Pregnancy
8.2 Labor and Delivery
8.3 Nursing Mothers
8.4 Pediatric Use
8.5 Geriatric Use
8.6 Hepatic Impairment
8.7 Renal Impairment
9. DRUG ABUSE AND DEPENDENCE
9.1 Controlled Substance
9.2 Abuse
9.3 Dependence
10. OVERDOSAGE
10.1 Signs and Symptoms
10.2 Treatment
11. DESCRIPTION
12. CLINICAL PHARMACOLOGY
12.1 Mechanism of Action
12.2 Pharmacodynamics
12.3 Pharmacokinetics
13. NONCLINICAL TOXICOLOGY
13.1 Carcinogenesis, Mutagenesis, Impairment of Fertility
16. HOW SUPPLIED/STORAGE AND HANDLING
16.1 How Supplied
16.2 Storage and Handling
17. PATIENT COUNSELING INFORMATION

*
Sections or subsections omitted from the full prescribing information are not listed.

1. INDICATIONS AND USAGE

Oxycodone Hydrochloride Oral Solution, USP is an immediate-release oral formulation of oxycodone hydrochloride indicated for the management of moderate to severe acute and chronic pain where the use of an opioid analgesic is appropriate.

2. DOSAGE AND ADMINISTRATION

Take care when prescribing and administering Oxycodone Hydrochloride Oral Solution, USP to avoid dosing errors due to confusion between mg and mL, which could result in accidental overdose and death. Take care to ensure the proper dose is communicated and dispensed. When writing prescriptions, include both the total dose in mg and the total dose in volume. Always use the enclosed calibrated oral syringe when administering Oxycodone Hydrochloride Oral Solution, USP to ensure the dose is measured and administered accurately.

Selection of patients for treatment with oxycodone hydrochloride should be governed by the same principles that apply to the use of similar opioid analgesics. Individualize treatment in every case, using non-opioid analgesics, opioids on an as needed basis and/or combination products, and chronic opioid therapy in a progressive plan of pain management such as outlined by the World Health Organization, the Agency for Healthcare Research and Quality, and the American Pain Society.

2.1 Individualization of Dosage

As with any opioid drug product, adjust the dosing regimen for each patient individually, taking into account the patient's prior analgesic treatment experience. In the selection of the initial dose of oxycodone hydrochloride, give attention to the following:

the total daily dose, potency and specific characteristics of the opioid the patient has been taking previously;
the reliability of the relative potency estimate used to calculate the equivalent oxycodone hydrochloride dose needed;
the patient's degree of opioid tolerance;
the general condition and medical status of the patient;
concurrent medications;
the type and severity of the patient's pain;
risk factors for abuse, addiction or diversion, including a prior history of abuse, addiction or diversion.

The following dosing recommendations, therefore, can only be considered suggested approaches to what is actually a series of clinical decisions over time in the management of the pain of each individual patient.

Continual re-evaluation of the patient receiving oxycodone hydrochloride is important, with special attention to the maintenance of pain control and the relative incidence of side effects associated with therapy. During chronic therapy, especially for non-cancer-related pain, periodically re-assess the continued need for the use of opioid analgesics.

During periods of changing analgesic requirements, including initial titration, frequent contact is recommended between physician, other members of the healthcare team, the patient, and the caregiver/family.

2.2 Initiation of Therapy

Start patients who have not been receiving opioid analgesics on Oxycodone Hydrochloride Oral Solution, USP in a dosing range of 5 to 15 mg every 4 to 6 hours as needed for pain.

Titrate the dose based upon the individual patient's response to their initial dose of Oxycodone Hydrochloride Oral Solution. Adjust the dose to an acceptable level of analgesia taking into account the improvement in pain intensity and the tolerability of the oxycodone by the patient.

2.3 Conversion to Oral Oxycodone Oral Solution

There is inter-patient variability in the potency of opioid drugs and opioid formulations. Therefore, a conservative approach is advised when determining the total daily dose of Oxycodone Hydrochloride. It is better to underestimate a patient's 24-hour oral Oxycodone Hydrochloride dose and make available rescue medication than to overestimate the 24-hour oral Oxycodone Hydrochloride dose and manage an adverse experience of overdose.

2.3.1 Conversion from Fixed-Ratio Opioid/Acetaminophen, Opioid/Aspirin, or Opioid/Nonsteroidal Combination Drugs

When converting patients from fixed ratio opioid/non-opioid drug regimens it may be necessary to titrate the dose of Oxycodone Hydrochloride Oral Solution, USP in response to the level of analgesia and adverse effects.

2.3.2 Conversion from Non-Oxycodone Opioids

In converting patients from other opioids to oxycodone hydrochloride, close observation and adjustment of dosage based upon the patient's response to oxycodone hydrochloride is imperative. Physicians and other healthcare professionals are advised to refer to published relative potency information, keeping in mind that conversion ratios are only approximate.

2.4 Conversion from Oral Oxycodone Hydrochloride to Controlled-Release Oral Oxycodone

The relative bioavailability of Oxycodone Hydrochloride Oral Solution, USP compared to controlled-release oxycodone is unknown, so conversion to controlled-release tablets must be accompanied by close observation for signs of excessive sedation.

2.5 Maintenance of Therapy

Continual re-evaluation of the patient receiving Oxycodone Hydrochloride Oral Solution, USP is important, with special attention to the maintenance of pain management and the relative incidence of side effects associated with therapy. If the level of pain increases, effort should be made to identify the source of increased pain, while adjusting the dose as described above to decrease the level of pain.

During chronic therapy, especially for non-cancer-related pain (or pain associated with other terminal illnesses), the continued need for the use of opioid analgesics should be re-assessed as appropriate.

2.6 Cessation of Therapy

When a patient no longer requires therapy with Oxycodone Hydrochloride Oral Solution, USP for the treatment of their pain, it is important that therapy be gradually discontinued over time to prevent the development of an opioid abstinence syndrome (narcotic withdrawal). In general, therapy can be decreased by 25% to 50% per day with careful monitoring for signs and symptoms of withdrawal [see DRUG ABUSE AND DEPENDENCE (9.3) section for description of the signs and symptoms of withdrawal]. If the patient develops these signs or symptoms, the dose should be raised to the previous level and titrated down more slowly, either by increasing the interval between decreases, decreasing the amount of change in dose, or both. It is not known at what dose of Oxycodone Hydrochloride Oral Solution that treatment may be discontinued without risk of the opioid abstinence syndrome.

2.7 Dosage in patients with Hepatic or Renal Impairment

Follow a conservative approach to dose initiation in patients with hepatic or renal impairment. Monitor patients closely and adjust dose based on clinical response.

3. DOSAGE FORMS AND STRENGTHS

Oxycodone Hydrochloride Oral Solution, USP, 5 mg per 5 mL is available in a 500 mL plastic bottle and 5 mL unit dose cup.

4. CONTRAINDICATIONS

Oxycodone Hydrochloride Oral Solution, USP is contraindicated in

patients with respiratory depression in the absence of resuscitative equipment.
any patient who has or is suspected of having paralytic ileus.
patients with acute or severe bronchial asthma or hypercarbia.
patients with known hypersensitivity to oxycodone, oxycodone salts, or any component of this product

5. WARNINGS AND PRECAUTIONS

5.1 Risk of Medication Errors

Use caution when prescribing, dispensing, and administering Oxycodone Hydrochloride Oral Solution to avoid dosing errors due to confusion between mg and mL, and other oxycodone solutions with different concentrations, which could result in accidental overdose and death. Use caution to ensure the dose is communicated clearly and dispensed accurately. Always use the enclosed calibrated measuring cup when administering Oxycodone Hydrochloride Oral Solution to ensure the dose is measured and administered accurately.

5.2 Respiratory Depression

Respiratory depression is the primary risk of Oxycodone Hydrochloride Oral Solution. Respiratory depression occurs most frequently in elderly or debilitated patients, and in those suffering from conditions accompanied by hypoxia, hypercapnia, or upper airway obstruction, in whom even moderate therapeutic doses may significantly decrease pulmonary ventilation, or following large initial doses in non-tolerant patients, or when opioids are given in conjunction with other agents that depress respiration.

Use Oxycodone Hydrochloride Oral Solution with extreme caution in patients with significant chronic obstructive pulmonary disease or cor pulmonale, and in patients having substantially decreased respiratory reserve (e.g., severe kyphoscoliosis), hypoxia, hypercapnia, or pre-existing respiratory depression. In such patients, even usual therapeutic doses of Oxycodone Hydrochloride Oral Solution may increase airway resistance and decrease respiratory drive to the point of apnea. Consider alternative non-opioid analgesics, and use Oxycodone Hydrochloride Oral Solution only under careful medical supervision at the lowest effective dose in such patients.

5.3 Misuse and Abuse of Opioids

Oxycodone Hydrochloride Oral Solution is a Schedule II controlled substance with an abuse liability similar to other opioids.

Such drugs are sought by drug abusers and people with addiction disorders. Diversion of Schedule II products is an act subject to criminal penalty.

Patients should be assessed for their clinical risks for opioid abuse or addiction prior to being prescribed opioids.

Oxycodone Hydrochloride Oral Solution can be abused in a manner similar to other opioid agonists, legal or illicit. This should be considered when prescribing or dispensing Oxycodone Hydrochloride Oral Solution in situations where the physician or pharmacist is concerned about an increased risk of misuse or abuse.

Oxycodone Hydrochloride Oral Solution may be abused by injecting the product. These practices pose a significant risk to the abuser that could result in overdose and death [see DRUG ABUSE AND DEPENDENCE (9.2) and OVERDOSAGE (10)].

Concerns about abuse, addiction, and diversion should not prevent the proper management of pain. Healthcare professionals should contact their State Professional Licensing Board or State Controlled Substances Authority for information on how to prevent and detect abuse or diversion of this product.

5.4 Interactions with Alcohol and Drugs of Abuse

Oxycodone Hydrochloride Oral Solution may be expected to have additive effects when used in conjunction with alcohol, other opioids, or illicit drugs that cause central nervous system depression because respiratory depression, hypotension, profound sedation, coma or death may result [see DRUG INTERACTIONS (7.1)].

5.5 Use in Head Injury and Increased Intracranial Pressure

In the presence of head injury, intracranial lesions or a preexisting increase in intracranial pressure, the possible respiratory depressant effects of Oxycodone Hydrochloride Oral Solution and its potential to elevate cerebrospinal fluid pressure (resulting from vasodilation following CO2 retention) may be markedly exaggerated. Furthermore, Oxycodone Hydrochloride Oral Solution can produce effects on pupillary response and consciousness, which may obscure neurologic signs of further increases in intracranial pressure in patients with head injuries.

5.6 Hypotensive Effect

Oxycodone Hydrochloride Oral Solution may cause severe hypotension in an individual whose ability to maintain blood pressure has been compromised by a depleted blood volume, or after concurrent administration with drugs such as phenothiazines or general anesthetics or other agents which compromise vasomotor tone. Oxycodone Hydrochloride Oral Solution may produce orthostatic hypotension in ambulatory patients. Administer Oxycodone Hydrochloride Oral Solution with caution in hypovolemic patients, such as those suffering acute myocardial infarction, because oxycodone may cause or further aggravate their hypotension. Administer Oxycodone Hydrochloride Oral Solution with caution to patients in circulatory shock, since vasodilatation produced by the drug may further reduce cardiac output and blood pressure.

5.7 Gastrointestinal Effects

Do not administer Oxycodone Hydrochloride Oral Solution to patients with gastrointestinal obstruction, especially paralytic ileus because oxycodone hydrochloride diminishes propulsive peristaltic waves in the gastrointestinal tract and may prolong the obstruction.

The administration of Oxycodone Hydrochloride Oral Solution may obscure the diagnosis or clinical course in patients with acute abdominal condition.

5.8 Use in Pancreatic/Biliary Tract Disease

Use Oxycodone Hydrochloride Oral Solution with caution in patients with biliary tract disease, including acute pancreatitis, as oxycodone hydrochloride may cause spasm of the sphincter of Oddi and diminish biliary and pancreatic secretions.

5.9 Special Risk Groups

Use Oxycodone Hydrochloride Oral Solution with caution and in reduced dosages in patients with severe renal or hepatic impairment, Addison's disease, hypothyroidism, prostatic hypertrophy, or urethral stricture, and in elderly or debilitated patients [see USE IN SPECIFIC POPULATIONS (8.5)] .

Exercise caution in the administration of Oxycodone Hydrochloride Oral Solution to patients with CNS depression, toxic psychosis, acute alcoholism and delirium tremens. All opioids may aggravate convulsions in patients with convulsive disorders, and all opioids may induce or aggravate seizures in some clinical settings.

Keep Oxycodone Hydrochloride Oral Solution out of the reach of children. In case of accidental ingestion, seek emergency medical help immediately.

5.10 Driving and Operating Machinery

Caution patients that oxycodone hydrochloride could impair the mental and/or physical abilities needed to perform potentially hazardous activities such as driving a car or operating machinery.

Caution patients about the potential combined effects of Oxycodone Hydrochloride Oral Solution with other CNS depressants, including other opioids, phenothiazines, sedative/hypnotics and alcohol [see DRUG INTERACTIONS (7)].

5.11 Cytochrome P450 3A4 Inhibitors and Inducers

Since the CYP3A4 isoenzyme plays a major role in the metabolism of oxycodone, drugs that alter CYP3A4 activity may cause changes in clearance of oxycodone which could lead to changes in oxycodone plasma concentrations. The expected clinical results with CYP3A4 inhibitors would be an increase in oxycodone plasma concentrations and possibly increased or prolonged opioid effects. The expected clinical results with CYP3A4 inducers would be a decrease in oxycodone plasma concentrations, lack of efficacy or, possibly, development of an abstinence syndrome in a patient who had developed physical dependence to oxycodone.

If co-administration is necessary, caution is advised when initiating Oxycodone Hydrochloride Oral Solution treatment in patients currently taking, or discontinuing, CYP3A4 inhibitors or inducers. Evaluate these patients at frequent intervals and consider dose adjustments until stable drug effects are achieved [see DRUG INTERACTIONS (7.4) and CLINICAL PHARMACOLOGY (12.3)].

5.12 Seizures

Oxycodone Hydrochloride Oral Solution may aggravate convulsions in patients with convulsive disorders, and all opioids may induce or aggravate seizures in some clinical settings.

6. ADVERSE REACTIONS

The following serious adverse reactions are described, or described in greater detail, in other sections:

Respiratory depression [see Warnings and Precautions (5.2)]
Seizures [see Warnings and Precautions (5.12)]
Hypotension [see Warnings and Precautions (5.6)]
Spasm of the sphincter of Oddi and increases in the serum amylase level [see Warnings and Precautions (5.8)]

Serious adverse reactions that may be associated with oxycodone therapy in clinical use are those observed with other opioid analgesics and include: respiratory depression, respiratory arrest, circulatory depression, cardiac arrest, hypotension, and/or shock [see Overdose (10.1) and Warnings and Precautions (5.1, 5.3)].

The less severe adverse events seen on initiation of therapy with oxycodone are also typical opioid side effects. These events are dose dependent, and their frequency depends on the clinical setting, the patient's level of opioid tolerance, and host factors specific to the individual. They should be expected and managed as a part of opioid analgesia. The most frequent of these include nausea, constipation, vomiting, headache, and pruritus.

In many cases the frequency of adverse events during initiation of opioid therapy may be minimized by careful individualization of starting dosage, slow titration and the avoidance of large rapid swings in plasma concentration of the opioid. Many of these adverse events will abate as therapy is continued and some degree of tolerance is developed, but others may be expected to remain throughout therapy.

Because clinical trials are conducted under widely varying conditions, adverse reaction rates observed in the clinical trials of a drug cannot be directly compared to rates in the clinical trials of another drug and may not reflect the rates observed in practice.

In all patients for whom dosing information was available (n=191) from the open-label and double-blind studies involving immediate-release oxycodone, the following adverse events were recorded in oxycodone treated patients with an incidence ≥ 3%. In descending order of frequency they were: nausea, constipation, vomiting, headache, pruritus, insomnia, dizziness, asthenia, and somnolence.

The following adverse experiences occurred in less than 3% of patients involved in clinical trials with oxycodone:

Body as a Whole: abdominal pain, accidental injury, allergic reaction, back pain, chills and fever, fever, flu syndrome, infection, neck pain, pain, photosensitivity reaction, and sepsis.

Cardiovascular: deep thrombophlebitis, heart failure, hemorrhage, hypotension, migraine, palpitation, and tachycardia.

Digestive: anorexia, diarrhea, dyspepsia, dysphagia, gingivitis, glossitis, and nausea and vomiting.

Hemic and Lymphatic: anemia and leukopenia.

Metabolic and Nutritional: edema, gout, hyperglycemia, iron deficiency anemia and peripheral edema.

Musculoskeletal: arthralgia, arthritis, bone pain, myalgia and pathological fracture.

Nervous: agitation, anxiety, confusion, dry mouth, hypertonia, hypesthesia, nervousness, neuralgia, personality disorder, tremor, and vasodilation.

Respiratory: bronchitis, cough increased, dyspnea, epistaxis, laryngismus, lung disorder, pharyngitis, rhinitis, and sinusitis.

Skin and Appendages: herpes simplex, rash, sweating, and urticaria.

Special Senses: amblyopia.

Urogenital: urinary tract infection

7. DRUG INTERACTIONS

7.1 CNS Depressants

Patients receiving narcotic analgesics, general anesthetics, phenothiazines, other tranquilizers, sedative-hypnotics or other CNS depressants (including alcohol) concomitantly with Oxycodone Hydrochloride Oral Solution may exhibit an additive CNS depression. Interactive effects resulting in respiratory depression, hypotension, profound sedation, or coma may result if these drugs are taken in combination with the usual dosage of Oxycodone Hydrochloride Oral Solution. When such combined therapy is contemplated, the dose of one or both agents should be reduced.

7.2 Neuromuscular Blocking Agents

Oxycodone may enhance the neuromuscular blocking action of skeletal muscle relaxants and produce an increased degree of respiratory depression.

7.3 Mixed Agonist/Antagonist Opioid Analgesics

Agonist/antagonist analgesics (i.e., pentazocine, nalbuphine, butorphanol and buprenorphine) should be administered with caution to patients who have received or are receiving a course of therapy with a pure opioid agonist analgesic such as Oxycodone Hydrochloride Oral Solution. In this situation, mixed agonist/antagonist analgesics may reduce the analgesic effect of Oxycodone Hydrochloride Oral Solution and/or may precipitate withdrawal symptoms in these patients.

7.4 Agents Affecting Cytochrome P450 Enzymes

CYP3A4 Inhibitors

A published study showed that the co-administration with voriconazole, a CYP3A4 inhibitor, significantly increased the plasma concentrations of oxycodone. Inhibition of CYP3A4 activity by its inhibitors, such as macrolide antibiotics (e.g., erythromycin), azole-antifungal agents (e.g., ketoconazole), and protease inhibitors (e.g., ritonavir), may prolong opioid effects. If co-administration is necessary, caution is advised when initiating therapy with, currently taking, or discontinuing CYP3A4 inhibitors. Evaluate these patients at frequent intervals and consider dose adjustments until stable drug effects are achieved [see Clinical Pharmacology (12.3)].

CYP3A4 Inducers

A published study showed that the co-administration of rifampin, a drug metabolizing enzyme inducer, significantly decreased plasma oxycodone concentrations. Induction of CYP3A4 activity by its inducers, such as rifampin, carbamazepine, and phenytoin, may lead to a lack of efficacy or, possibly, development of an abstinence syndrome in a patient who had developed physical dependence to oxycodone. If co-administration is necessary, caution is advised when initiating therapy with, currently taking, or discontinuing CYP3A4 inducers. Evaluate these patients at frequent intervals and consider dose adjustments until stable drug effects are achieved [see Clinical Pharmacology (12.3)].

CYP2D6 Inhibitors

Oxycodone is metabolized in part to oxymorphone via the Cytochrome P450 Isoenzyme CYP2D6. While this pathway may be blocked by a variety of drugs (e.g., certain cardiovascular drugs and antidepressants), such blockade has not yet been shown to be of clinical significance with this agent. However, clinicians should be aware of this possible interaction.

7.5 Monoamine Oxidase Inhibitors (MAOIs)

MAOIs have been reported to intensify the effects of at least one opioid drug, causing anxiety, confusion and significant depression of respiration or coma. The use of Oxycodone Hydrochloride Oral Solution is not recommended for patients taking MAOIs or within 14 days of stopping such treatment.

7.6 Anticholinergics

Anticholinergics or other medications with anticholinergic activity, when used concurrently with opioid analgesics including oxycodone hydrochloride, may result in increased risk of urinary retention and/or severe constipation, which may lead to paralytic ileus.

8. USE IN SPECIFIC POPULATIONS

8.1 Pregnancy

Pregnancy Category B: There are no adequate and well-controlled studies of oxycodone use during pregnancy. Based on limited human data in the literature, oxycodone does not appear to increase the risk of congenital malformations. Because animal reproduction studies are not always predictive of human response, oxycodone should be used during pregnancy only if clearly needed.

Teratogenic Effects

Reproduction studies in Sprague-Dawley rats and New Zealand rabbits revealed that oxycodone administered orally at doses up to 16 mg/kg (approximately 2 times the daily oral dose of 90 mg for adults on a mg/m2 basis) and 25 mg/kg (approximately 5 times the daily oral dose of 90 mg on a mg/m2 basis), respectively was not teratogenic or embryo-fetal toxic.

Nonteratogenic Effects

Neonates whose mothers have taken oxycodone chronically may exhibit respiratory depression and/or withdrawal symptoms, either at birth and/or in the nursery.

8.2 Labor and Delivery

Oxycodone Hydrochloride Oral Solution, USP is not recommended for use in women during or immediately prior to labor. Opioids cross the placenta and may produce respiratory depression and psycho-physiologic effects in neonates. Occasionally, opioid analgesics may prolong labor through actions which temporarily reduce the strength, duration and frequency of uterine contractions. Neonates, whose mothers received opioid analgesics during labor, should be observed closely for signs of respiratory depression. A specific narcotic antagonist, naloxone, should be available for reversal of narcotic-induced respiratory depression in the neonate.

8.3 Nursing Mothers

Low levels of oxycodone have been detected in maternal milk. The amount of oxycodone hydrochloride delivered to the infant depends on the plasma concentration of the mother, the amount of milk ingested by the infant, and the extent of first-pass metabolism. Because of the potential for serious adverse reactions in nursing infants from oxycodone hydrochloride including respiratory depression, sedation and possibly withdrawal symptoms, upon cessation of oxycodone hydrochloride administration to the mother, decide whether to discontinue nursing or to discontinue the drug, taking into account the importance of the drug to the mother.

8.4 Pediatric Use

The safety and efficacy of Oxycodone Hydrochloride Oral Solution, USP in pediatric patients below the age of 18 have not been established.

8.5 Geriatric Use

Elderly patients (aged 65 years or older) may have increased sensitivity to oxycodone hydrochloride. In general, use caution when selecting a dose for an elderly patient, usually starting at the low end of the dosing range, reflecting the greater frequency of decreased hepatic, renal, or cardiac function and of concomitant disease or other drug therapy.

8.6 Hepatic Impairment

Since oxycodone is extensively metabolized, its clearance may decrease in hepatic failure patients. Follow a conservative approach to dose initiation in patients with hepatic impairment, monitor patients closely and adjust the dose based on clinical response.

8.7 Renal Impairment

Information from oxycodone tablets indicate that patients with renal impairment (defined as a creatinine clearance <60 mL/min) had higher plasma concentrations of oxycodone than subjects with normal renal function. Use a conservative approach to dose initiation in patients with renal impairment, monitor patients closely and adjust the dose based on clinical response.

9. DRUG ABUSE AND DEPENDENCE

9.1 Controlled Substance

Oxycodone hydrochloride is a mu-agonist opioid of the morphine type and is a Schedule II controlled substance. Oxycodone Hydrochloride Oral Solution, USP, like other opioids used in analgesia, can be abused and is subject to criminal diversion.

9.2 Abuse

Drug addiction is characterized by compulsive use, use for non-medical purposes, and continued use despite harm or risk of harm. Drug addiction is a treatable disease, utilizing a multi-disciplinary approach, but relapse is common.

"Drug-seeking" behavior is very common in addicts and drug abusers. Drug-seeking tactics include emergency calls or visits near the end of office hours, refusal to undergo appropriate examination, testing or referral, repeated "loss" of prescriptions, tampering with prescriptions and reluctance to provide prior medical records or contact information for other treating physician(s). "Doctor shopping" to obtain additional prescriptions is common among drug abusers and people suffering from untreated addiction.

The risks of misuse and abuse should be considered when prescribing or dispensing Oxycodone Hydrochloride Oral Solution, USP. Concerns about abuse and addiction, should not prevent the proper management of pain, however. Treatment of pain should be individualized, balancing the potential benefits and risks for each patient.

Abuse and addiction are separate and distinct from physical dependence and tolerance. Physicians should be aware that addiction may not be accompanied by concurrent tolerance and symptoms of physical dependence. In addition, abuse of opioids can occur in the absence of true addiction and is characterized by misuse for nonmedical purposes, often in combination with other psychoactive substances. Careful record-keeping of prescribing information, including quantity, frequency, and renewal requests is strongly advised.

Oxycodone Hydrochloride Oral Solution, USP is intended for oral use only. Abuse of Oxycodone Hydrochloride Oral Solution poses a risk of overdose and death. The risk is increased with concurrent abuse of alcohol and other substances. Parenteral drug abuse is commonly associated with transmission of infectious diseases such as hepatitis and HIV.

Proper assessment of the patient, proper prescribing practices, periodic re-evaluation of therapy, and proper dispensing and storage are appropriate measures that help to limit abuse of opioid drugs.

Infants born to mothers physically dependent on opioids will also be physically dependent and may exhibit respiratory difficulties and withdrawal symptoms [see Use in Specific Populations (8.2)].

9.3 Dependence

Tolerance to opioids is demonstrated by the need for increasing doses of opioids to maintain a defined effect such as analgesia (in the absence of disease progression or other external factors). If tolerance develops, or if pain severity increases, a gradual increase in dose may be required. The first sign of tolerance is usually a reduced duration of effect. Tolerance to different effects of opioids may develop to varying degrees and at varying rates in a given individual. There is also inter-patient variability in the rate and extent of tolerance that develops to various opioid effects, whether the effect is desirable (e.g., analgesia) or undesirable (e.g., nausea). Physical dependence is manifested by withdrawal symptoms after abrupt discontinuation of a drug or upon administration of an antagonist. Physical dependence and tolerance are frequent during chronic opioid therapy.

Patients using Oxycodone Hydrochloride Oral Solution, USP chronically (for several weeks) should be instructed that they should contact their health care providers if they notice the need to increase dosing to treat symptoms of pain or they experience symptoms of withdrawal upon abrupt cessation of dosing.

The opioid abstinence or withdrawal syndrome is characterized by some or all of the following: restlessness, lacrimation, rhinorrhea, yawning, perspiration, chills, myalgia, and mydriasis. Other symptoms also may develop, including irritability, anxiety, backache, joint pain, weakness, abdominal cramps, insomnia, nausea, anorexia, vomiting, diarrhea, or increased blood pressure, respiratory rate, or heart rate.

In general, taper opioids rather than abruptly discontinue [see Dosage and Administration (2.6)].

10. OVERDOSAGE

10.1 Signs and Symptoms

Acute overdose with Oxycodone Hydrochloride Oral Solution, USP can be manifested by respiratory depression (a decrease in respiratory rate and/or end tidal volume. Cheyne-Stokes respiration, cyanosis), extreme somnolence progressing to stupor or coma, skeletal muscle flaccidity, cold and clammy skin, constricted pupils, bradycardia, hypotension, pulmonary edema, cardiac arrest, and death.

Oxycodone Hydrochloride Oral Solution, USP may cause miosis, even in total darkness. Pinpoint pupils are a sign of opioid overdose but are not pathognomonic (e.g., pontine lesions of hemorrhagic or ischemic origin may produce similar findings). Marked mydriasis rather than miosis may be seen with hypoxia in overdose situations [see Clinical Pharmacology (12)] .

10.2 Treatment

Give primary attention to the reestablishment of a patent airway and institution of assisted or controlled ventilation. Supportive measures including oxygen and vasopressors should be employed in the management of circulatory shock and pulmonary edema accompanying overdose as indicated. Cardiac arrest or arrhythmias may require cardiac massage or defibrillation.

The pure opioid antagonists, naloxone or nalmefene, are specific antidotes to respiratory depression resulting from opioid overdose. Since the duration of reversal is expected to be less than the duration of action of oxycodone hydrochloride, carefully monitor the patient until spontaneous respiration is reliably re-established. If the response to opioid antagonists is suboptimal or only brief in nature, administer additional antagonist as directed by the manufacturer of the product.

Do not administer opioid antagonists in the absence of clinically significant respiratory or circulatory depression secondary to oxycodone overdose. Administer such agents cautiously to persons who are known, or suspected to be physically dependent on oxycodone. In such cases, an abrupt or complete reversal of opioid effects may precipitate an acute abstinence syndrome.

In an individual physically dependent on opioids, administration of the usual dose of the antagonist will precipitate an acute withdrawal syndrome. The severity of the withdrawal symptoms experienced will depend on the degree of physical dependence and the dose of the antagonist administered. Reserve use of an opioid antagonist for cases where such treatment is clearly needed. If it is necessary to treat serious respiratory depression in the physically dependent patient, initiate administration of the antagonist with care and titrate with smaller than usual doses.

11. DESCRIPTION

Oxycodone Hydrochloride Oral Solution, USP, 5mg/5mL: Each 5 mL's is for oral administration and contains 5 mg of oxycodone hydrochloride USP.

Oxycodone hydrochloride is a white, odorless crystalline powder derived from the opium alkaloid, thebaine. Oxycodone hydrochloride dissolves in water (1 g in 6 to 7 mL) and is considered slightly soluble in alcohol (octanol water partition coefficient is 0.7).

Chemically, oxycodone hydrochloride is 4, 5α-epoxy-14-hydroxy-3-methoxy-17-methylmorphinan-6-one hydrochloride and has the following structural formula:

[Structure]

The 5 mg per 5 mL Oxycodone Hydrochloride Oral Solution contains equivalent of 4.5 mg of oxycodone free base per 5 mL's and contains the following inactive ingredients: Poloxamer 188 NF, Sodium Benzoate NF, Citric Acid Anhydrous USP, Glycerin USP, Sorbitol Solution 70% USP, FD&C Red #40 , Raspberry Flavor and Water.

12. CLINICAL PHARMACOLOGY

12.1 Mechanism of Action

Oxycodone, as the hydrochloride salt, is a full opioid agonist whose principal therapeutic action is analgesia.

12.2 Pharmacodynamics

Effects on Central Nervous System

Specific CNS opioid receptors for endogenous compounds with opioid-like activity have been identified throughout the brain and spinal cord and play a role in the analgesic effects of this drug. A significant feature of opioid-induced analgesia is that it occurs without loss of consciousness. The relief of pain by morphine-like opioids is relatively selective, in that other sensory modalities, (e.g., touch, vibrations, vision, hearing, etc.) are not obtunded.

Oxycodone produces respiratory depression by direct action on brain stem respiratory centers. The respiratory depression involves both a reduction in the responsiveness of the brain stem respiratory centers to increases in carbon dioxide tension and to electrical stimulation.

Oxycodone depresses the cough reflex by direct effect on the cough center in the medulla. Antitussive effects may occur with doses lower than those usually required for analgesia. Oxycodone causes miosis, even in total darkness. Pinpoint pupils are a sign of opioid overdose but are not pathognomonic (e.g., pontine lesions of hemorrhagic or ischemic origins may produce similar findings). Marked mydriasis rather than miosis may be seen due to hypoxia in overdose situations.

Effects on Gastrointestinal Tract and Other Smooth Muscle

Oxycodone, like other opioid analgesics, produces some degree of nausea and vomiting which is caused by direct stimulation of the chemoreceptor trigger zone (CTZ) located in the medulla. The frequency and severity of emesis gradually diminishes with time.

Oxycodone may cause a decrease in the secretion of hydrochloric acid in the stomach that reduces motility while increasing the tone of the antrum, stomach, and duodenum. Digestion of food in the small intestine is delayed and propulsive contractions are decreased. Propulsive peristaltic waves in the colon are decreased, while tone may be increased to the point of spasm resulting in constipation. Other opioid-induced effects may include a reduction in biliary and pancreatic secretions, spasm of sphincter of Oddi, and transient elevations in serum amylase.

Cardiovascular System

Oxycodone, in therapeutic doses, produces peripheral vasodilatation (arteriolar and venous), decreased peripheral resistance, and inhibits baroreceptor reflexes. Manifestations of histamine release and/or peripheral vasodilatation may include pruritus, flushing, red eyes, sweating, and/or orthostatic hypotension.

Endocrine System

Opioid agonists have been shown to have a variety of effects on the secretion of hormones. Opioids inhibit the secretion of ACTH, cortisol, and luteinizing hormone (LH) in humans. They also stimulate prolactin, growth hormone (GH) secretion, and pancreatic secretion of insulin and glucagon in humans and other species, rats and dogs. Thyroid stimulating hormone (TSH) has been shown to be both inhibited and stimulated by opioids.

Immune System

Opioids have been shown to have a variety of effects on components of the immune system in in vitro and animal models. The clinical significance of these findings is unknown.

12.3 Pharmacokinetics

The activity of Oxycodone Hydrochloride Oral Solution is primarily due to the parent drug oxycodone.

Absorption

The oral bioavailability of oxycodone is 60 - 87%. This high oral bioavailability (compared to other oral opioids) is due to lower pre-systemic and/or first-pass metabolism of oxycodone.

Food Effect

Presence of food may slightly delay the rate (Cmax and Tmax) and enhance the extent of absorption (AUC) of oxycodone from Oxycodone Hydrochloride Oral Solution. Overall, food is not expected to have a clinically significant impact on the absorption of Oxycodone Hydrochloride Oral Solution.

Distribution

Following intravenous administration, the volume of distribution (Vss) for oxycodone was 2.6 L/kg. Plasma protein binding of oxycodone at 37°C and a pH of 7.4 was about 45%. Oxycodone has been found in breast milk [see USE IN SPECIFIC POPULATIONS (8.3)].

Metabolism

Oxycodone hydrochloride is extensively metabolized to noroxycodone, oxymorphone, noroxymorphone, which are subsequently glucuronidated. CYP3A4 mediated N-demethylation to noroxycodone is the primary metabolic pathway of oxycodone with a less contribution from CYP2D6 mediated O-demethylation to oxymorphone. Therefore, the formation of these and related metabolites can, in theory, be affected by other drugs. The major circulating metabolite is noroxycodone with an AUC ratio of 0.6 relative to that of oxycodone. Noroxycodone is reported to be a considerably weaker analgesic than oxycodone. Oxymorphone, although possessing analgesic activity, is present in the plasma only in low concentrations. The correlation between oxymorphone concentrations and opioid effects was much less than that seen with oxycodone plasma concentrations. The analgesic activity profile of other metabolites is not known.

Excretion

Oxycodone and its metabolites are excreted primarily via the kidney. The amounts measured in the urine have been reported as follows: free oxycodone up to 19%; conjugated oxycodone up to 50%; free oxymorphone 0%; conjugated oxymorphone ≤ 14%; both free and conjugated noroxycodone have been found in the urine but not quantified. The total plasma clearance was 0.8 L/min for adults. Apparent elimination half-life of oxycodone following the administration of Oxycodone Hydrochloride Oral Solution was approximately 3.5 hours.

Special Populations

Geriatric

Information obtained from oxycodone tablets indicate that the plasma concentrations of oxycodone did not appear to be increased in patients over of the age of 65.

Gender

Information obtained from oxycodone tablets support the lack of gender effect on the pharmacokinetics of oxycodone.

Hepatic Impairment

Since oxycodone is extensively metabolized, its clearance may be decreased in hepatic failure patients [see Use in Special Populations (8.6)].

Renal Impairment

Information obtained from oxycodone tablets indicate that patients with renal impairment (defined as creatinine clearance < 60 mL/min) had higher plasma concentrations of oxycodone than subjects with normal renal function [see USE IN SPECIAL POPULATIONS (8.7)].

Drug-Drug Interactions

CYP3A4 Inhibitors

CYP3A4 is the major enzyme involved in noroxycodone formation. A published study showed that the co-administration of voriconazole, a CYP3A4 inhibitor, increased oxycodone AUC and Cmax by 3.6 and 1.7 fold, respectively.

CYP3A4 Inducers

A published study showed that the co-administration of rifampin, a drug metabolizing enzyme inducer, decreased oxycodone AUC and Cmax values by 86% and 63%, respectively.

CYP2D6 Inhibitors

Oxycodone is metabolized in part to oxymorphone via the cytochrome p450 isoenzyme CYP2D6. While this pathway may be blocked by a variety of drugs (e.g., certain cardiovascular drugs and antidepressants), such blockade has not yet been shown to be of clinical significance with this agent.

13. NONCLINICAL TOXICOLOGY

13.1 Carcinogenesis, Mutagenesis, Impairment of Fertility

Carcinogenesis

Long-term animal studies to evaluate the carcinogenic potential of oxycodone have not been conducted.

Mutagenesis

Oxycodone hydrochloride was genotoxic in an in vitro mouse lymphoma assay in the presence of metabolic activation. There was no evidence of genotoxic potential in an in vitro bacterial reverse mutation assay (Salmonella typhimurium and Escherichia coli) or in an assay for chromosomal aberrations (in vivo mouse bone marrow micronucleus assay).

Impairment of Fertility

The potential effects of oxycodone on male and female fertility have not been evaluated.

16. HOW SUPPLIED/STORAGE AND HANDLING

16.1 How Supplied

Oxycodone Hydrochloride Oral Solution, USP, 5 mg per 5 mL is available as follows:

NDC 60432-706-05: 500 mL plastic bottle packaged with calibrated measuring cup

16.2 Storage and Handling

All opioids, including Oxycodone Hydrochloride Oral Solution, USP, are liable to diversion and misuse both by the general public and healthcare workers and should be handled accordingly.

Dispense in a tight, light-resistant container as defined in the USP/NF.

Keep in secured area and protect from diversion.

Store at controlled room temperature 20°-25°C (68°- 77°F).

17. PATIENT COUNSELING INFORMATION

See MEDICATION GUIDE

Provide the following information to patients receiving Oxycodone Hydrochloride Oral Solution, USP or their caregivers:
Advise patients that Oxycodone Hydrochloride Oral Solution, USP is a narcotic pain medication, and should be taken only as directed.
Advise patients that sharing oxycodone can result in fatal overdose and death.
Advise patients that Oxycodone Hydrochloride Oral Solution, USP is a potential drug of abuse. They must protect it from theft. It should never be given to anyone other than the individual for whom it was prescribed.
Advise patients to keep Oxycodone Hydrochloride Oral Solution, USP in a secure place out of the reach of children. When Oxycodone Hydrochloride Oral Solution, USP is no longer needed, the unused solution should be destroyed by flushing down the toilet.
Advise patients how to measure and take the correct dose of Oxycodone Hydrochloride Oral Solution, and to always use the enclosed calibrated measuring cup when administering Oxycodone Hydrochloride Oral Solution, USP, to ensure the dose is measured and administered accurately.
Advise patients whenever the prescribed concentration is changed to avoid dosing errors which could result in accidental overdose and death.
Advise patients not to adjust the dose of Oxycodone Hydrochloride Oral Solution, USP without consulting with a physician or other healthcare professional.
Advise patients that Oxycodone Hydrochloride Oral Solution, USP may cause drowsiness, dizziness, or lightheadedness and may impair mental and/or physical ability required for the performance of potentially hazardous tasks (e.g., driving, operating machinery). Advise patients started on Oxycodone Hydrochloride Oral Solution, USP or patients whose dose has been adjusted to refrain from any potentially dangerous activity until it is established that they are not adversely affected.
Advise patients that Oxycodone Hydrochloride Oral Solution, USP will add to the effect of alcohol and other CNS depressants (such as antihistamines, sedatives, hypnotics, tranquilizers, general anesthetics, phenothiazines, other opioids, and monoamine oxidase [MAO] inhibitors).
Advise patients not to combine Oxycodone Hydrochloride Oral Solution, USP with central nervous system depressants (sleep aids, tranquilizers) except by the orders of the prescribing physician, and not to combine with alcohol because dangerous additive effects may occur, resulting in serious injury or death.
Advise women of childbearing potential who become or are planning to become pregnant to consult a physician prior to initiating or continuing therapy with Oxycodone Hydrochloride Oral Solution, USP.
Advise patients that safe use in pregnancy has not been established and that prolonged use of opioid analgesics including Oxycodone Hydrochloride Oral Solution, USP during pregnancy may cause fetal-neonatal physical dependence, and neonatal withdrawal may occur.
If patients have been receiving treatment with Oxycodone Hydrochloride Oral Solution, USP for more than a few weeks and cessation of therapy is indicated, counsel them on the importance of safely tapering the dose and that abruptly discontinuing the medication could precipitate withdrawal symptoms. Provide a dose schedule to accomplish a gradual discontinuation of the medication.
Advise patients taking Oxycodone Hydrochloride Oral Solution, USP of the potential for severe constipation; appropriate laxatives and/or stool softeners as well as other appropriate treatments should be initiated from the onset of opioid therapy.
Advise patients of the most common adverse events that may occur while taking Oxycodone Hydrochloride Oral Solution, USP: constipation, nausea, somnolence, lightheadedness, dizziness, sedation, vomiting, and sweating.
Advise patients to call 911 or the local Poison Control center, and get emergency help immediately if they take more Oxycodone Hydrochloride Oral Solution, USP than prescribed, or overdose.
Advise patients, that if they miss a dose, to take the missed dose as soon as possible. If it is almost time for the next dose, skip the missed dose and go back to their regular dosing schedule. Do not take two doses at once unless instructed by their healthcare provider.

DEA Order Form Required

Manufactured For:

Wockhardt USA, LLC.

Parsippany, NJ 07054

Manufactured By:

Morton Grove Pharmaceuticals, Inc.

Morton Grove, IL 60053

For more information about Oxycodone Hydrochloride Oral Solution, go to www.wockhardtusa.com or call Wockhardt USA, LLC at 1-800-346-6854.

28706

Rev.06-15

MEDICATION GUIDE

Oxycodone Hydrochloride (ox-ee-CO-dohn) (CII)Oral Solution, USP

IMPORTANT: Keep Oxycodone Hydrochloride Oral Solution, USP in a safe place away from children. Accidental use by a child is a medical emergency and
can cause death. If a child accidentally takes Oxycodone Hydrochloride Oral Solution, USP, get emergency help right away.

Read the Medication Guide that comes with Oxycodone Hydrochloride Oral Solution, USP before you start taking it and each time you get a new prescription. There may be new information. This Medication Guide does not take the place of talking to your healthcare provider about your medical condition or your treatment.

What Is The Most Important Information I Should Know About Oxycodone Hydrochloride Oral Solution?

Oxycodone Hydrochloride Oral Solution can cause serious side effects, including death.

Take Oxycodone Hydrochloride Oral Solution exactly as prescribed by your healthcare provider. If you take the wrong dose or strength of Oxycodone Hydrochloride Oral Solution, you could overdose and die.
It is especially important when you take Oxycodone Hydrochloride Oral Solution that you know exactly what dose and strength to take, and the right way to measure your medicine. Your healthcare provider or pharmacist should show you the right way to measure your medicine. Always use the dosing cup provided with Oxycodone Hydrochloride Oral Solution to help make sure you measure the right amount.
Do not drink alcohol. Using alcohol with Oxycodone Hydrochloride Oral Solution may increase your risk of dangerous side effects, including death.

What is Oxycodone Hydrochloride Oral Solution?

Oxycodone Hydrochloride Oral Solution is in a group of drugs called narcotic pain medicine. Oxycodone Hydrochloride Oral Solution is only for adults who have moderate to severe pain.

A prescription medicine that is used to manage moderate to severe pain that is expected to last a short period of time (acute), and pain that continues around-the-clock and is expected to last for a long period of time (chronic).
Oxycodone Hydrochloride Oral Solution is a federally controlled substance (CII) because it is a strong opioid pain medicine that can be abused by people who abuse prescription medicines or street drugs.
Prevent theft, misuse or abuse. Keep Oxycodone Hydrochloride Oral Solution in a safe place to keep it from being stolen. Oxycodone Hydrochloride Oral Solution can be a target for people who misuse or abuse prescription medicines or street drugs.
Never give Oxycodone Hydrochloride Oral Solution to anyone else, even if they have the same symptoms you have. It may harm them or even cause death.
Selling or giving away this medicine is against the law.
It is not known if Oxycodone Hydrochloride Oral Solution is safe and effective in children under age 18 years of age.

Who Should Not Take Oxycodone Oral Solution?

Do not take Oxycodone if you:

are having breathing problems and there is no emergency medical equipment nearby
have a bowel blockage called paralytic ileus
are having an asthma attack or have severe asthma, trouble breathing, or lung problems
are allergic to oxycodone or any of the ingredients in Oxycodone Hydrochloride Oral Solution. See the end of this Medication Guide for a complete list of ingredients in Oxycodone Hydrochloride Oral Solution

What should I tell my healthcare provider before taking Oxycodone Hydrochloride Oral Solution?

Before taking Oxycodone Hydrochloride Oral Solution, tell your healthcare provider if you:

have trouble breathing or lung problems
have had a head injury
have liver or kidney problems
have adrenal gland problems, such as Addison's disease
have severe scoliosis that affects your breathing
have thyroid problems
have problems urinating or enlargement of your prostate
have or had convulsions or seizures
have a past or present drinking problem or alcoholism
have hallucinations (seeing or hearing things that are not really there) or other severe mental problems
have constipation or other bowel problems
have problems with your pancreas or gallbladder
have past or present substance abuse or drug addiction
have any other medical conditions
are pregnant or plan to become pregnant. It is not known if Oxycodone Hydrochloride Oral Solution will harm your unborn baby. Talk to your healthcare provider if you are pregnant or plan to become pregnant.

If you take Oxycodone Hydrochloride Oral Solution regularly before your baby is born, your newborn baby may have signs of withdrawal because their body has become used to the medicine. Signs of withdrawal in a newborn baby can include:

○ irritability
○ being very active
○ problems sleeping
○ high pitched cry
○ vomiting
○ diarrhea or more stools than normal
○ weight loss
○ shaking (tremors)

If you are taking Oxycodone Hydrochloride Oral Solution right before your baby is born, your baby could have breathing problems.

are breast-feeding or plan to breastfeed. Some Oxycodone Hydrochloride Oral Solution passes into your breast milk. A nursing baby could become very sleepy or have difficulty breathing or feeding well. If you stop breastfeeding, your baby may have withdrawal symptoms. See the list of withdrawal symptoms above. You and your healthcare provider should decide if you will take Oxycodone Hydrochloride Oral Solution or breastfeed.

Tell your healthcare provider about all the medicines you take, including prescription and non-prescription medicines, vitamins, and herbal supplements. Sometimes the doses of medicines that you take with Oxycodone Hydrochloride Oral Solution may need to be changed if used together. Be especially careful about taking other medicines that make you sleepy such as:

sleeping pills
other pain medicines
anti-nausea medicines
tranquilizers
muscle relaxants
anti-anxiety medicines
antihistamines
anti-depressants
monoamine oxidase inhibitors (MAOIs): Do not take Oxycodone Hydrochloride Oral Solution if you already take an MAOI or within 14 days after you stop taking an MAOI medicine

Ask your healthcare provider if you are not sure if your medicine is one listed above.

Do not take other medicines while using Oxycodone Hydrochloride Oral Solution until you have talked with your healthcare provider or pharmacist. They will tell you if it is safe to take other medicines with Oxycodone Hydrochloride Oral Solution.

Know the medicines you take. Keep a list of them and show it to your healthcare provider and pharmacist when you get a new medicine.

How Should I Take Oxycodone?

See "What is the most important information I should know about Oxycodone Hydrochloride Oral Solution?"

Take Oxycodone Hydrochloride Oral Solution exactly as prescribed. Do not change your dose unless your healthcare provider tells you to. Your healthcare provider may change your dose after seeing how the medicine affects you. Call your healthcare provider if your pain is not well controlled with your prescribed dose of Oxycodone Hydrochloride Oral Solution.
Make sure you understand exactly how to measure your dose. Always use the dosing cup provided with our Oxycodone Hydrochloride Oral Solution to help make sure you measure the right amount. See the Patient Instructions for Use at the end of this Medication Guide for information about how to measure your dose the right way. Ask your healthcare provider or pharmacist if you are not sure what dose of Oxycodone Hydrochloride Oral Solution you should take or if you are not sure how to use the dosing cup.
Do not stop taking Oxycodone Hydrochloride Oral Solution suddenly. If you have been taking Oxycodone Hydrochloride Oral Solution for more than a few weeks, stopping it suddenly can make you sick with withdrawal symptoms (for example, nausea, vomiting, diarrhea, anxiety, and shivering). If your healthcare provider decides you no longer need Oxycodone Hydrochloride Oral Solution, ask how to slowly reduce this medicine. Do not stop taking Oxycodone Hydrochloride Oral Solution without talking to your healthcare provider.
If you miss a dose, take it as soon as possible. If it is almost time for your next dose, skip the missed dose and go back to your regular dosing schedule. Do not take 2 doses at one time unless your healthcare provider tells you to.
If you take too much Oxycodone Hydrochloride Oral Solution call your healthcare provider or your local Poison Control Center right away or go to the nearest hospital emergency room right away.
Talk with your healthcare provider regularly about your pain to see if you still need to take Oxycodone Hydrochloride Oral Solution.

What Should I Avoid While Taking Oxycodone?

You should not drink alcohol while using Oxycodone Hydrochloride Oral Solution. Drinking alcohol with Oxycodone Hydrochloride Oral Solution may increase your risk of having dangerous side effects or death.
Do not drive, operate heavy machinery, or do other dangerous activities, especially when you start taking Oxycodone Hydrochloride Oral Solution and when your dose is changed, until you know how Oxycodone Hydrochloride Oral Solution affects you. Oxycodone can make you sleepy. Ask your healthcare provider to tell you when it is okay to do these activities.

What are the Possible Side Effects of Oxycodone?

Oxycodone Hydrochloride Oral Solution can cause serious side effects, including:
See "What is the most important information I should know about Oxycodone Hydrochloride Oral Solution?"
Oxycodone can cause serious breathing problems that can become life-threatening, especially if Oxycodone Hydrochloride Oral Solution is used the wrong way. Call your healthcare provider or get help right away if:

○ your breathing slows down

○ you have shallow breathing (little chest movement with breathing)

○ you feel faint, dizzy, confused, or

○ you have any other unusual symptoms

These can be symptoms that you have taken too much Oxycodone Hydrochloride Oral Solution (overdose) or the dose is too high for you. These symptoms may lead to serious problems or death if not treated right away.

Oxycodone Hydrochloride Oral Solution can cause your blood pressure to drop. This can make you feel dizzy if you get up too fast from sitting or lying down. Low blood pressure is also more likely to happen if you take other medicines that can also lower your blood pressure. Severe low blood pressure can happen if you lose blood or take certain other medicines.
Oxycodone can cause physical dependence. Do not stop taking Oxycodone or any other opioid without talking to your healthcare provider about how to slowly stop your medicine. You could become sick with uncomfortable withdrawal symptoms because your body has become used to these medicines. Physical dependence is not the same as drug addiction. Tell your healthcare provider if you have any of these symptoms of withdrawal while slowly stopping Oxycodone:

○ feel restless
○ tearing eyes
○ sweating
○ chills or hair on your arms "stand up"
○ muscle aches, backache
○ dilated pupils of your eyes
○ feel irritable or anxious
○ trouble sleeping
○ runny nose
○ yawning
○ nausea, loss of appetite, vomiting
○ diarrhea, stomach area (abdominal) cramps
○ increase in your blood pressure
○ breathing faster, or your heart beats faster

There is a chance of abuse or addiction with Oxycodone Hydrochloride Oral Solution. The chance is higher if you are or have been addicted to or abused other medicines, street drugs, or alcohol, or if you have a history of mental problems.
Seizures: Oxycodone Hydrochloride Oral Solution may cause seizures or make seizures that you already have worse.

Call your healthcare provider if you have any of the symptoms listed above.

Common side effects of Oxycodone Hydrochloride Oral Solution include:

○ nausea
○ constipation
○ vomiting
○ headache
○ itching
○ trouble sleeping
○ dizziness
○ weakness
○ drowsiness
○ sweating
○ light headedness

Constipation (not often enough or hard bowel movements) is a very common side effect of pain medicines (opioids) including Oxycodone Hydrochloride Oral Solution. Talk to your healthcare provider about dietary changes, and the use of laxatives (medicines to treat constipation) and stool softeners to prevent or treat constipation while taking Oxycodone Hydrochloride Oral Solution.

Tell your healthcare provider if you have any side effect that bothers you or that does not go away.

These are not all the possible side effects of Oxycodone Hydrochloride Oral Solution. For more information, ask your healthcare provider or pharmacist.

Call your doctor for medical advice about side effects. You may report side effects to FDA at 1-800-FDA-1088.

How should I store Oxycodone Hydrochloride Oral Solution?

Store Oxycodone Hydrochloride Oral Solution at controlled room temperature between 68°F - 77°F (20°C - 25°C).
Protect Oxycodone Hydrochloride Oral Solution from moisture and light.
When Oxycodone Hydrochloride Oral Solution is no longer needed, the unused solution should be destroyed by flushing down the toilet.

Keep Oxycodone Hydrochloride Oral Solution out of the reach of children. Accidental overdose by a child is a medical emergency and can lead to death.

General information about Oxycodone Hydrochloride Oral Solution

Medicines are sometimes prescribed for purposes other than those listed in a Medication Guide. Do not use Oxycodone Hydrochloride Oral Solution for a condition for which it was not prescribed.

Do not give your Oxycodone Hydrochloride Oral Solution to other people, even if they have the same symptoms you have. Selling or giving away Oxycodone Hydrochloride Oral Solution may harm others, may cause death, and is against the law.

This Medication Guide summarizes the most important information about Oxycodone Hydrochloride Oral Solution. If you would like more information, talk with your healthcare provider. You can ask your healthcare provider or pharmacist for information about Oxycodone Hydrochloride Oral Solution that is written for healthcare professionals.

For more information about Oxycodone Hydrochloride Oral Solution, go to www.wockhardtusa.com or call Wockhardt USA, LLC at 1-800-346-6854.

What are the ingredients in Oxycodone Hydrochloride Oral Solution?

Active ingredient: oxycodone hydrochloride

Inactive ingredients: anhydrous citric acid, FD&C red #40, glycerin, poloxamer 188, purified water, raspberry flavor, sodium benzoate and sorbitol solution.

This Medication Guide has been approved by the U.S. Food and Drug Administration.

Rev.11-13

Manufactured For:

Wockhardt USA, LLC.

Parsippany, NJ 07054

Manufactured By:

Morton Grove Pharmaceuticals, Inc.

Morton Grove, IL 60053

Rx Only

28706A